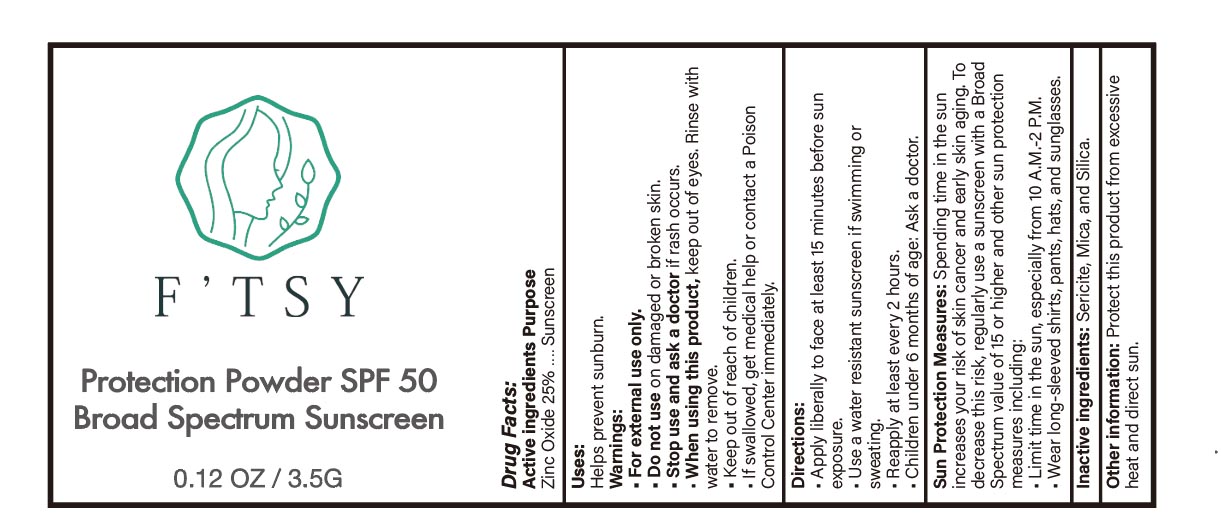 DRUG LABEL: sunscreen powder
NDC: 83447-001 | Form: POWDER
Manufacturer: Guangzhou Fantesy Biotechnology Co.,Ltd
Category: otc | Type: HUMAN OTC DRUG LABEL
Date: 20260105

ACTIVE INGREDIENTS: ZINC OXIDE 25 g/100 g
INACTIVE INGREDIENTS: SILICON DIOXIDE; MICA; PYROPHYLLITE

83447-001

Active ingredients

Zinc Oxide 25%

Purpose

Sunscreen

Uses

Helps prevent sunburn

Warnings

For external use only.
Do not use on damaged or broken skin.
Stop use and ask a doctor if rash occurs.
When using this product, keep out of eyes. Rinse with water to remove.
Keep out of reach of children.
If swallowed, get medical help or contact a Poison Control Center immediately.

Do not use on damaged or broken skin.

When using this product, keep out of eyes. Rinse with water to remove.

Stop use

Stop use and ask a doctor if rash occurs.

Keep out of reach of children.

Directions

Apply liberally to face at least 15 minutes before sun exposure.
Use a water resistant sunscreen if swimming or sweating.
Reapply at least every 2 hours.
Children under 6 months of age: Ask a doctor

Other information

Protect this product from excessive heat and direct sun.

Inactive ingredients

Sericite, Mica, and Silica.